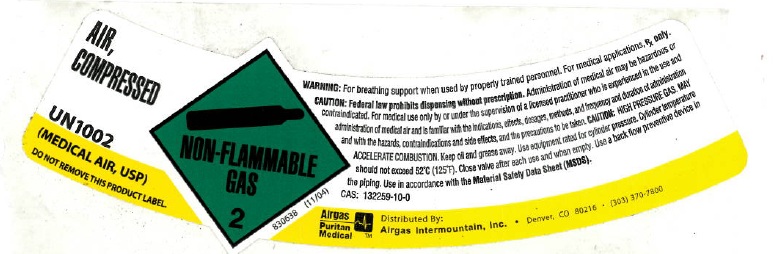 DRUG LABEL: Air
NDC: 58420-005 | Form: GAS
Manufacturer: Airgas Intermountain Inc
Category: prescription | Type: HUMAN PRESCRIPTION DRUG LABEL
Date: 20100902

ACTIVE INGREDIENTS: Air 1000 mL/1 L

air

PACKAGE LABEL

AIR, COMPRESSED
UN1002
(MEDICAL AIR, USP)
DO NOT REMOVE THIS PRODUCT LABEL
NON-FLAMMABLE 2
830638 (11/04)
WARNING: For breathing support when used by properly trained personnel. For medical applications, Rx only. CAUTION: Federal law prohibits dispensing without a prescription. WARNING: Administration of medical air may be hazardous or contraindicated. For use only by or under the supervision of a licensed practitioner who is experienced in the use and administration of medical air, and is familiar with the indications, effects, dosages, methods, and frequency and duration of administration, and with the hazards, contraindications and side effects, and the precautions to be taken.
CAUTION: HIGH PRESSURE GAS. MAY ACCELERATE COMBUSTION. Keep oil and grease away. Use equipment rated for cylinder pressure. Cylinder temperature should not exceed 52oC(125oF). Close valve after each use and when empty. Use a back flow preventive device in the piping. Use in accordance with the Material Safety Data Sheet (MSDS).
CAS: 132259-10-0
AIRGAS PURITAN MEDICAL Distributed By: Airgas Intermountain, Inc. Denver, CO 80216 (303) 370-7800